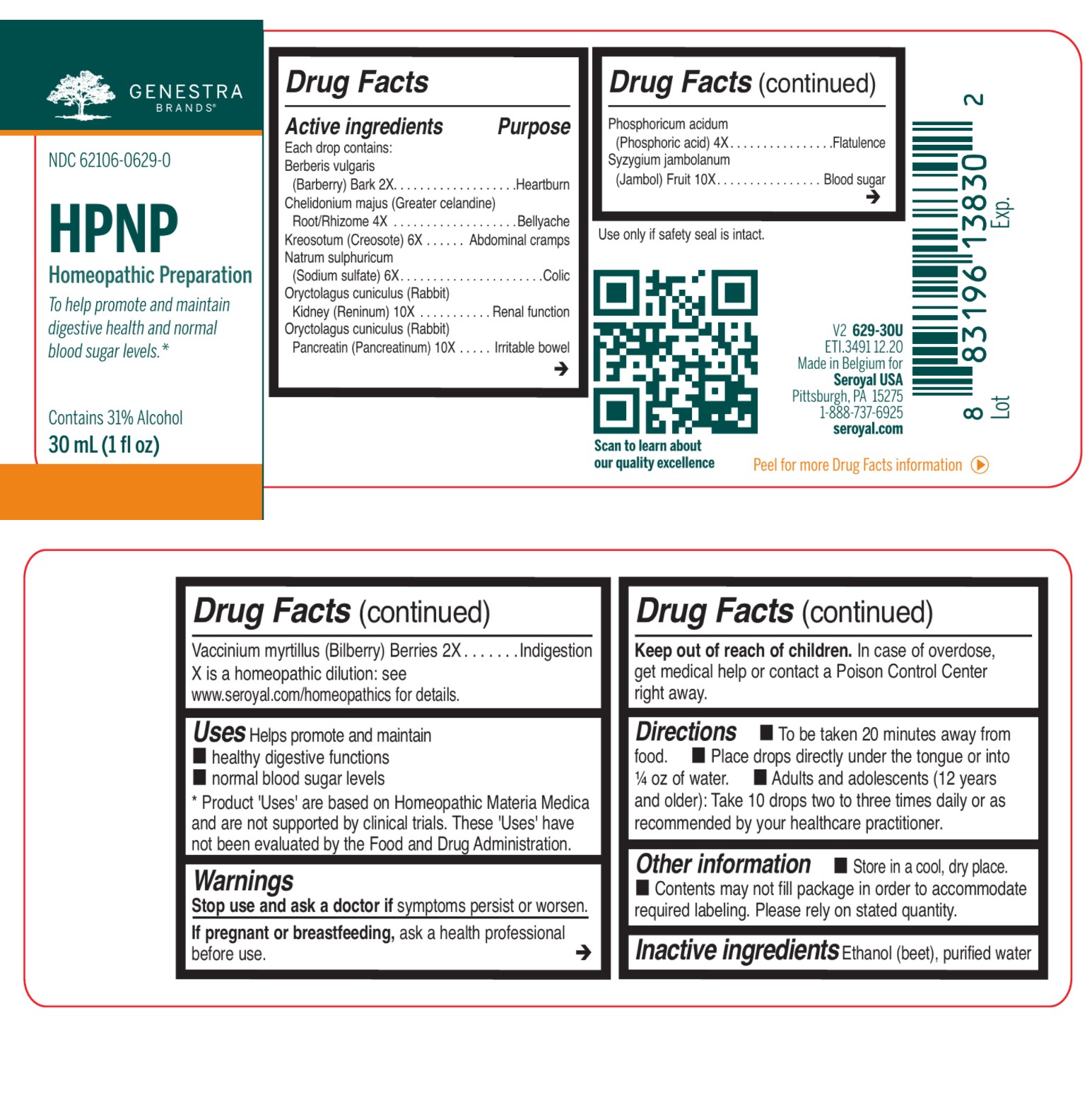 DRUG LABEL: HPNP
NDC: 62106-0629 | Form: LIQUID
Manufacturer: Seroyal USA
Category: homeopathic | Type: HUMAN OTC DRUG LABEL
Date: 20210722

ACTIVE INGREDIENTS: SODIUM SULFATE 6 [hp_X]/30 mL; ORYCTOLAGUS CUNICULUS KIDNEY 10 [hp_X]/30 mL; PHOSPHORIC ACID 4 [hp_X]/30 mL; BERBERIS VULGARIS ROOT BARK 2 [hp_X]/30 mL; CHELIDONIUM MAJUS ROOT 4 [hp_X]/30 mL; WOOD CREOSOTE 6 [hp_X]/30 mL; ORYCTOLAGUS CUNICULUS PANCREATIN 10 [hp_X]/30 mL; SYZYGIUM CUMINI FRUIT 10 [hp_X]/30 mL; BILBERRY 2 [hp_X]/30 mL
INACTIVE INGREDIENTS: WATER; ALCOHOL

HPNP

Active ingredients
Each drop contains:
Berberis vulgaris (Barberry) Bark 2X
Chelidonium majus (Greater celandine) Root/Rhizome 4X
Kreosotum (Creosote) 6X
Natrum sulphuricum (Sodium sulfate) 6X
Oryctolagus cuniculus (Rabbit) Kidney (Reninum) 10X
Oryctolagus cuniculus (Rabbit) Pancreatin (Pancreatinum) 10X

Phosphoricum acidum (Phosphoric acid) 4X
Syzygium jambolanum (Jambol seed) Fruit 10X

Vaccinium myrtillus (Bilberry) Berries 2X

Uses

Helps promote and maintain healthy digestive functions and normal blood sugar levels.

Warnings
Stop use and ask a doctor if symptoms persist or worsen.
If pregnant or breastfeeding, ask a health professional
before use.

Keep out of reach of children. In case of overdose,
get medical help or contact a Poison Control Center
right away

Keep out of reach of children. In case of overdose,
get medical help or contact a Poison Control Center
right away

PREGNANCY OR BREAST FEEDING

If pregnant or breastfeeding, ask a health professional
before use.

Other information

Use only if safety seal is intact.

Contents may not fill package in order to accommodate required labeling. Please rely on stated quantity.

Directions

To be taken 20 minutes away from food.

Place drops directly under the tongue or into ¼ oz of water.

Adults and adolescents (12 years and older): Take 10 drops two to three times daily or as
recommended by your healthcare practitioner.
Children (under 12 years): Take under the direction of your healthcare practitioner.

Uses

Helps promote and maintain healthy digestive functions and normal blood sugar levels.

Directions

To be taken 20 minutes away from food.

Place drops directly under the tongue or into ¼ oz of water.

Adults and adolescents (12 years and older): Take 10 drops two to three times daily or as
recommended by your healthcare practitioner.
Children (under 12 years): Take under the direction of your healthcare practitioner.

Inactive ingredients

Ethanol (beet), purified water

PACKAGE LABEL

NDC 62106-0629-0

HPNP

HOMEOPATHIC PREPARATION

To help promote and maintain

digestive health and normal

blood sugar levels.

Contains 31% Alcohol

1 fl oz (30 mL)